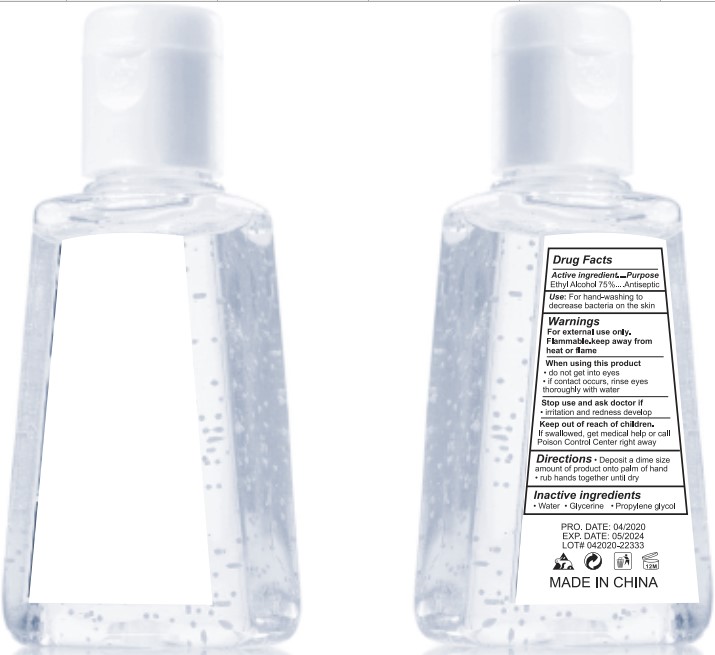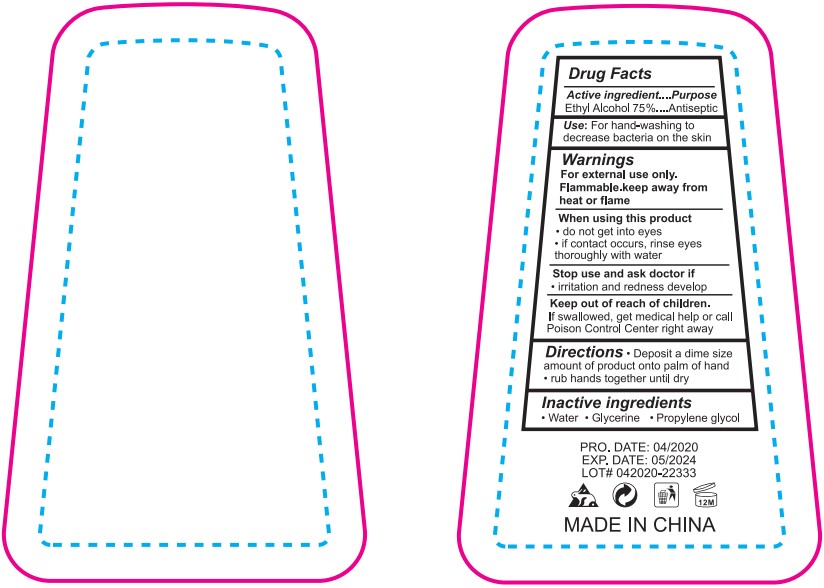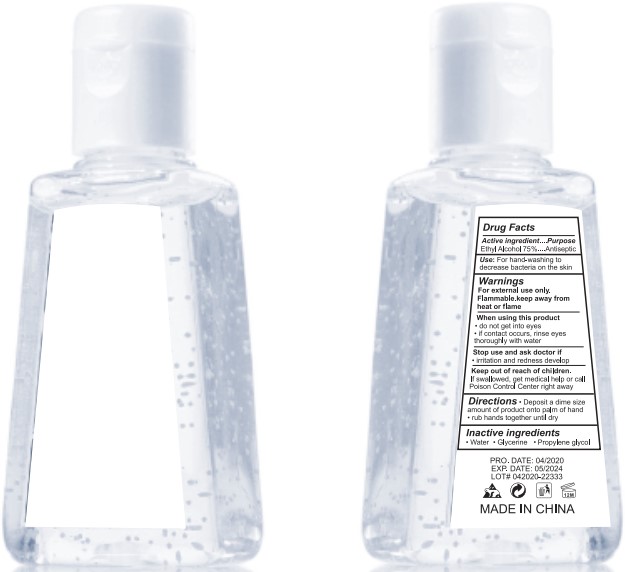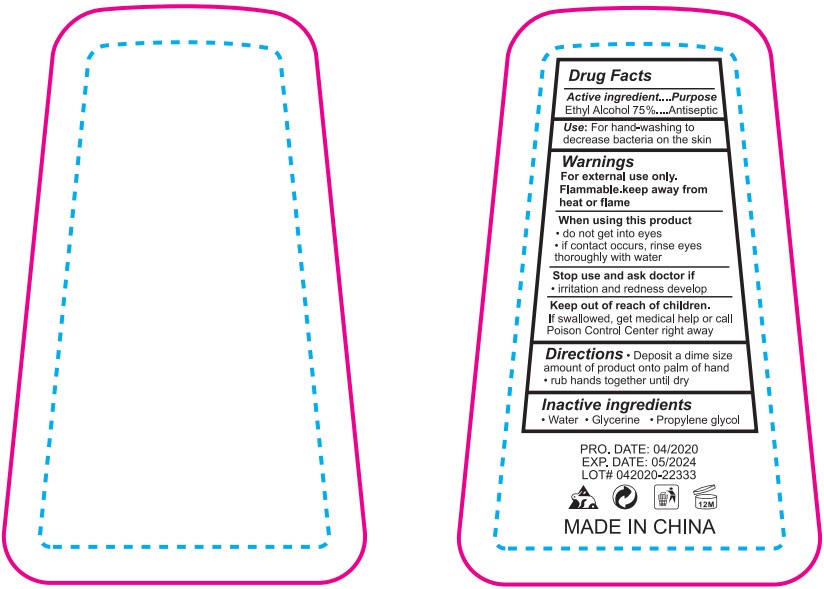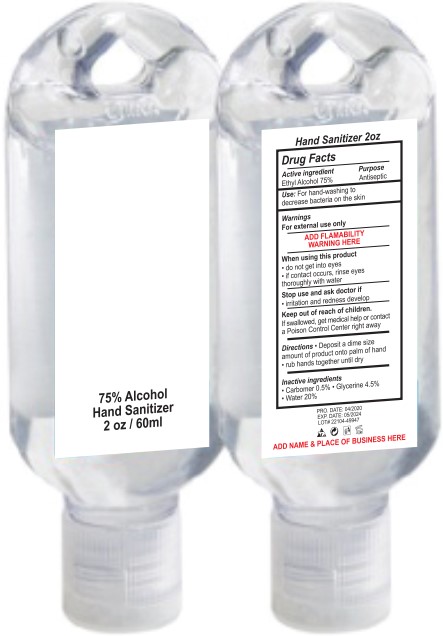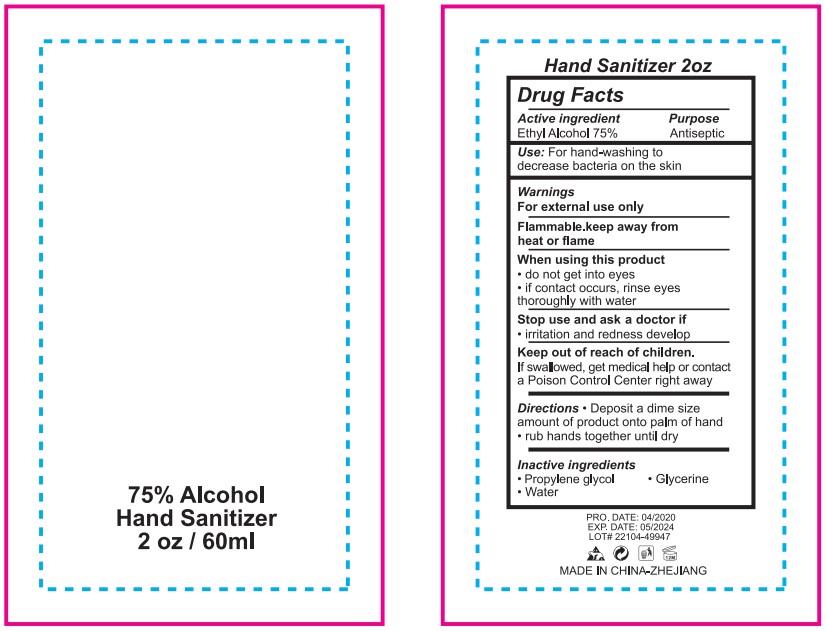 DRUG LABEL: 75% Alcohol Hand Sanitizer
NDC: 72922-014 | Form: SOLUTION
Manufacturer: Shangrao Chunyu Technology Co.,ltd.
Category: otc | Type: HUMAN OTC DRUG LABEL
Date: 20200707

ACTIVE INGREDIENTS: ALCOHOL 75 mL/100 mL
INACTIVE INGREDIENTS: PROPYLENE GLYCOL 0.5 mL/100 mL; GLYCERIN 0.5 mL/100 mL; CARBOMER 980 0.3 mL/100 mL; WATER 23.5 mL/100 mL; AMINOMETHYLPROPANOL 0.2 mL/100 mL

Active Ingredient(s)

Alcohol 75% v/v. Purpose: Antiseptic

Purpose

Antiseptic, Hand Sanitizer

Use

For hand-washing to decrease bacteria on the skin.

Warnings

For external use only. Flammable. Keep away from heat or flame.

When using this product keep out of eyes, ears, and mouth. In case of contact with eyes, rinse eyes thoroughly with water.
Stop use and ask a doctor if irritation or rash occurs. These may be signs of a serious condition.
Keep out of reach of children. If swallowed, get medical help or contact a Poison Control Center right away.

Do not use

Stop use and ask doctor if irritation and redness develop.

Keep out of reach of children. If swallowed, get medical help or call Poison Control Center right away.

Directions

- Deposit a dime size amount of product onto palm of hand.
- Rub hands together until dry.

Inactive ingredients

Aminomethylpropanol, carbopol 980 polymer, glycerin, propylene glycol, sterile distilled water.

Package Label - Principal Display Panel

30mL NDC: 72922-014-01

Package Label - Principal Display Panel

60 mL NDC: 72922-014-02

Package Label - Principal Display Panel

29 mL NDC: 72922-014-03